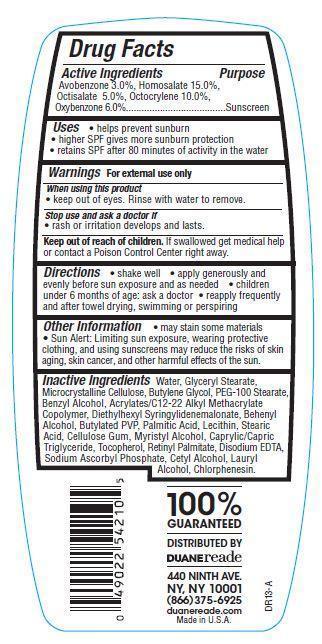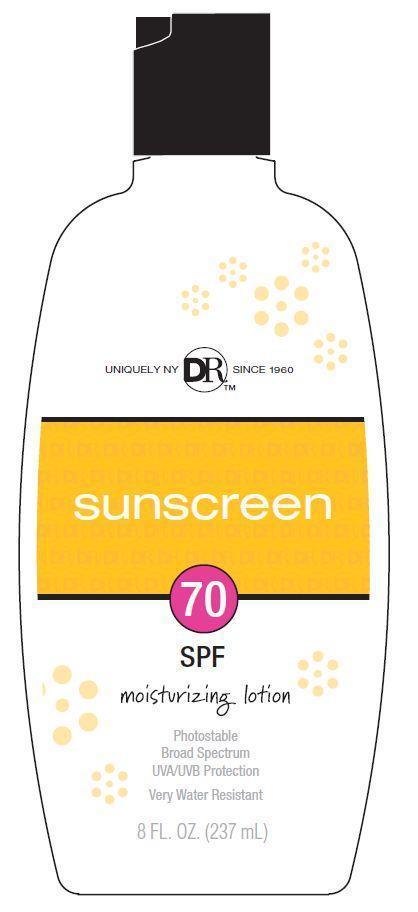 DRUG LABEL: Duane Reade Sunscreen
NDC: 67732-409 | Form: LOTION
Manufacturer: DUANE READE INC.
Category: otc | Type: HUMAN OTC DRUG LABEL
Date: 20121114

ACTIVE INGREDIENTS: AVOBENZONE 3 g/100 g; HOMOSALATE 15 g/100 g; OCTISALATE 5 g/100 g; OCTOCRYLENE 10 g/100 g; OXYBENZONE 6 g/100 g
INACTIVE INGREDIENTS: WATER; GLYCERYL MONOSTEARATE; STEARIC ACID; CELLULOSE, MICROCRYSTALLINE; BUTYLENE GLYCOL; PEG-100 STEARATE; BENZYL ALCOHOL; DIETHYLHEXYL SYRINGYLIDENEMALONATE; DOCOSANOL; PALMITIC ACID; CARBOXYMETHYLCELLULOSE SODIUM; TOCOPHEROL; EDETATE DISODIUM; MYRISTYL ALCOHOL; TRICAPRYLIN; VITAMIN A PALMITATE; SODIUM ASCORBYL PHOSPHATE; CETYL ALCOHOL; LAURYL ALCOHOL; CHLORPHENESIN

Drug Facts

Active Ingredients

Avobenzone 3.0 %

Homosalate 15.0%

Octisalate 5.0%

Octocrylene 10.0%

Oxybenzone 6.0%

Purpose

Sunscreen

Uses

- helps prevent sunburn
- higher SPF gives more sunburn protection
- retains SPF after 80 minutes of activity in the water

Warnings

For external use only

When using this product

- keep out of eyes. Rinse with water to remove.

stop use and ask a doctor if

- rash or irritation develops and lasts

Keep out of reach of children.

If swallowed get medical help or contact a Poison Control Center right away.

Directions

- shake well
- apply generously and evenly before sun exposure and as needed
- children under 6 months of age:ask a doctor
- reapply frequently and after towel drying, swimming or perspiring

Other Information

- may stain some materials
- Sun Alert: Limiting sun exposure, wearing protective clothing, and using sunscreens may reduce the risk of skin agin, skin cancer, and other harmful effects of the sun.

Inactive Ingredients

Water, Glyceryl Stearate, Microcrystalline Cellulose, Butylene Glcyol, PEG_100 Stearate, Benzyl Alcohol, Acrylates/C12-22 Alkyl Methcrylate Copolymer, Diethylhexyl Syringylidenemalonate, Behenyl Alcohol, Butylated PVP, Palmitic Acid, Lecithin, Stearic Acid, Cellulose Gum, Myristyl Alcohol, Caprylic/Capric Triglyceride, Tocopherol, Retinyl Palmitate, Disodium EDTA, Sodium Ascorbyl Phosphate, Cetyl Alcohol, Lauryl Alcohol, Chlorphenesin.

Principal Display Panel

UNIQUELY NY DRTM SINCE 1960
sunscreen
70
SPF
moisturizing lotion
Photostable
Broad Spectrum
UVA/UVB Protection
Very Water Resistant
8 FL.OZ.(237 mL)